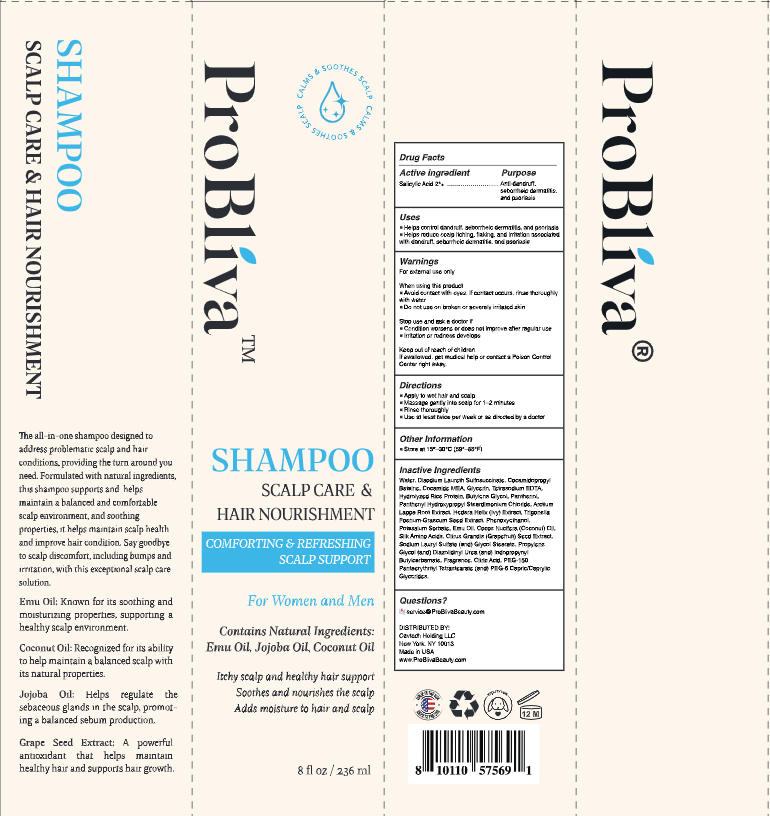 DRUG LABEL: ProBliva Anti Fungal Shampoo.
NDC: 85464-003 | Form: SHAMPOO
Manufacturer: CAVTECH HOLDING LLC
Category: otc | Type: HUMAN OTC DRUG LABEL
Date: 20260105

ACTIVE INGREDIENTS: SALICYLIC ACID 4.72 g/236 g
INACTIVE INGREDIENTS: GLYCERIN; CITRUS GRANDIS (GRAPEFRUIT) PEEL OIL; DIAZOLIDINYL UREA; BUTYLENE GLYCOL; COCAMIDE MEA; PANTHENOL; PROPYLENE GLYCOL; POTASSIUM SORBATE; ARCTIUM LAPPA WHOLE; WATER; COCAMIDOPROPYL BETAINE; SODIUM LAURYL SULFATE; IODOPROPYNYL BUTYLCARBAMATE; DISODIUM LAURETH SULFOSUCCINATE; PEG-150 PENTAERYTHRITYL TETRASTEARATE; PEG-6 CAPRYLIC/CAPRIC GLYCERIDES; TRIGONELLA FOENUM-GRAECUM FRUIT; HYDROLYZED RICE PROTEIN (ENZYMATIC; 2000 MW); GLYCOL STEARATE; TETRASODIUM EDTA; HEDERA HELIX (IVY) LEAF WATER; CITRIC ACID; GLYCERETH-7 CAPRYLATE/CAPRATE; SILK AMINO ACIDS; PANTHENYL HYDROXYPROPYL STEARDIMONIUM CHLORIDE; PHENOXYETHANOL; EMU OIL; COCOS NUCIFERA (COCONUT) OIL

Initial Drug Listing - ProBliva Anti-Fungal Shampoo

ACTIVE INGREDIENT

Salicylic Acid 2%

PURPOSE

Anti-dandruff,seborrheic dermatitis,and psoriasis

DOSAGE AND ADMINISTRATION

- Helps control dandruff, seborrheic dermatitis, and psoriasism
- Helps reduce scalp itching, flaking, and irritation associatedwith dandruff,seborrheic dermatitis, and psoriasis

WARNINGS

For external use only

WHEN USING

- Avoid contact with eyes. lf contact occurs, rinse thoroughly with water
- Do not use on broken or severely irritated skin

ASK DOCTOR

- Condition worsens or does not improve after regular use
- lrritation or redness develops

KEEP OUT OF REACH OF CHILDREN

If swallowed, get medical help or contact a Poison Control Center right away.

INDICATIONS AND USAGE

- Apply to wet hair and scalp
- Massage gently into scalp for 1-2 minutes
- Rinse thoroughly
- Use at least twice per week or as directed by a doctor

OTHER SAFETY INFORMATION

Store at 15°_30°C (59°-86°F)

INACTIVE INGREDIENT

Water, Disodium Laureth Sulfosuccinate,Cocamidopropyl Betaine, Cocamide MEA, Glycerin,Tetrasodium EDTA, Hydrolyzed Rice Protein, Butylene Glycol, Panthenol,Pantheny Ilydroxypropyl Steardimo-nium Chloride,Aretium Lappa Root Extract,Hedera Helix(Ivy) Extract,Trigonella Foenum-Graecum Seed Extract,Phenoxyethanol, Potassium Sorbate,Emu Oi, Cocos Nucifera(Coconut)Oil,Silk Amino Acids,Citrus Grandis (Grapefruit) Seed Extract, Sodium Lauryl Sulfate, Glycol Stearate, Panthenol, PropyleneGlycol,Diazolidinyl Urea, lodopropyny Butylcarbamate, Fragrance, Ciuric Acid,PEG-150 Pentaerythrityl tetrastearate (and)PEG-6 Capric/Caprylic glycerides

QUESTIONS

service@ProBlivaBeauty.com